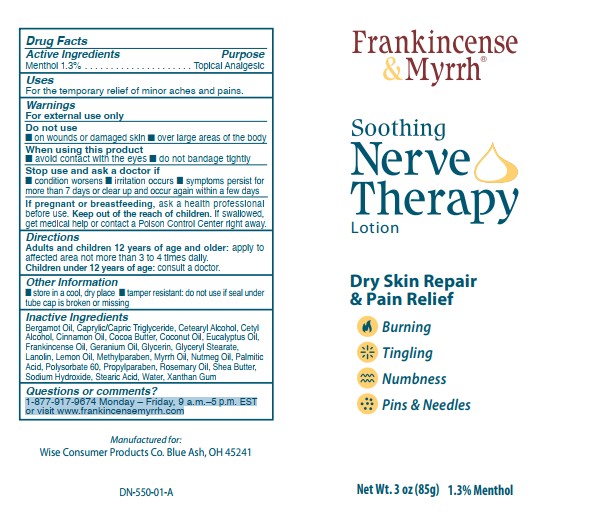 DRUG LABEL: Soothing Nerve Therapy
NDC: 42346-550 | Form: LOTION
Manufacturer: Wise Consumer Products
Category: otc | Type: HUMAN OTC DRUG LABEL
Date: 20251020

ACTIVE INGREDIENTS: MENTHOL 1.3 g/100 g
INACTIVE INGREDIENTS: LANOLIN; ROSEMARY OIL; XANTHAN GUM; WATER; CAPRYLIC/CAPRIC TRIGLYCERIDE; CETEARYL ALCOHOL; SHEA BUTTER; STEARIC ACID; LEMON OIL; GLYCERYL STEARATE; MYRRH OIL; SODIUM HYDROXIDE; FRANKINCENSE OIL; NUTMEG OIL; BERGAMOT OIL; GLYCERIN; METHYLPARABEN; POLYSORBATE 60; PROPYLPARABEN; CINNAMON OIL; EUCALYPTUS OIL; CETYL ALCOHOL; COCOA BUTTER; COCONUT OIL; GERANIUM OIL, ALGERIAN TYPE; PALMITIC ACID

Soothing Nerve Therapy Lotion

Active ingredients

Menthol 1.3%

Purpose

Menthol 1.3%......................Topical Analgesic

Uses

For the temporary relief of minor aches and pains.

Warnings

For external use only

When using this product

- avoid contact with the eyes
- do not bandage tightly

Do not use

- on wounds or damaged skin
- over large areas of the body

Stop use and ask a doctor if

- condition worsens
- irritation occurs
- symptoms persist for more than 7 days or clear up and occur again within a few days

PREGNANCY OR BREAST FEEDING

If pregnant or breastfeeding, ask a health professional before use.

KEEP OUT OF REACH OF CHILDREN

Keep out of the reach of children. If swallowed, get medical help or contact a Poison Control Center right away.

Directions

Adults and children 12 years of age and older: apply to affected area not more than 3 to 4 times daily.

Children under 12 years of age: consult a doctor.

Other information

- store in a cool, dry place
- tamper resistant: do not use if seal undertube cap is broken or missing

Inactive ingredients

Bergamot Oil, Caprylic/Capric Triglyceride, Cetearyl Alcohol, Cetyl Alcohol, Cinnamon Oil, Cocoa Butter, Coconut Oil, Eucalyptus Oil, Frankincense Oil, Geranium Oil, Glycerin, Glyceryl Stearate, Lanolin, Lemon Oil, Methylparaben, Myrrh Oil, Nutmeg Oil, Palmitic Acid, Polysorbate 60, Propylparaben, Rosemary Oil, Shea Butter, Sodium Hydroxide, Stearic Acid, Water, Xanthan Gum

Questions or comments?

1-877-917-9674 Monday – Friday, 9 a.m.–5 p.m. ESTor visit www.frankincensemyrrh.com

PACKAGE LABEL

Frankincense & Myrrh

Soothing Nerve Therapy

Lotion

Dry Skin Repair & Pain Relief

Burning

Tingling

Numbness

Pins & Needles

Net Wt. 3 oz (85g) 1.3% Menthol